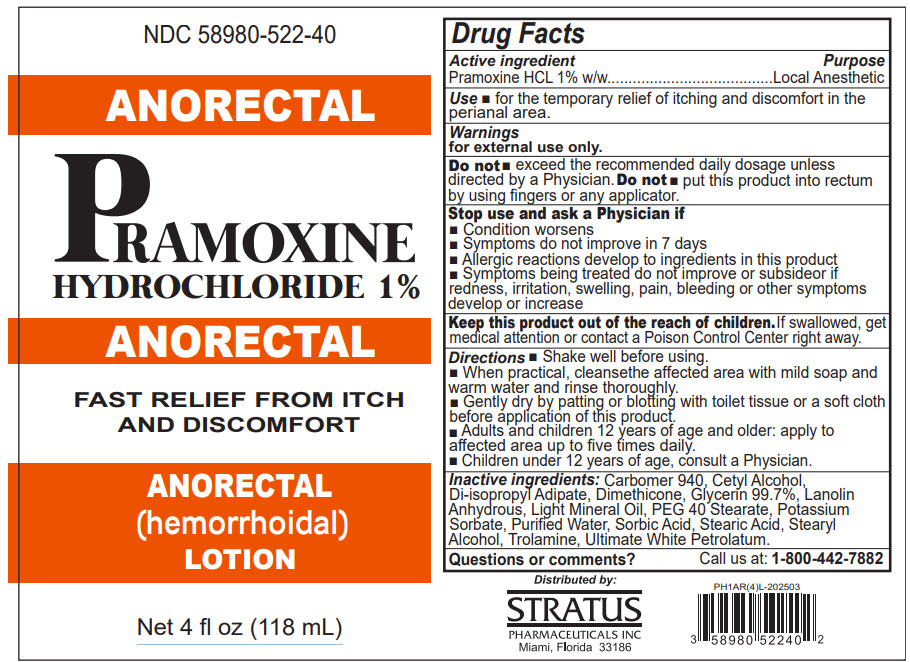 DRUG LABEL: Pramoxine Hydrochloride Anorectal
NDC: 58980-522 | Form: LOTION
Manufacturer: Stratus Pharmaceuticals
Category: otc | Type: HUMAN OTC DRUG LABEL
Date: 20251002

ACTIVE INGREDIENTS: Pramoxine Hydrochloride 1 mg/1 mL
INACTIVE INGREDIENTS: CARBOMER HOMOPOLYMER TYPE C (ALLYL PENTAERYTHRITOL CROSSLINKED); CETYL PALMITATE; Glycerin; Light Mineral Oil; WHITE PETROLATUM; STEARIC ACID; TROLAMINE; PEG-40 MONOSTEARATE; Stearyl Alcohol; LANOLIN; POTASSIUM SORBATE; DIISOPROPYL ADIPATE; Sorbic Acid; Water

Pramoxine Hydrochloride 1% Anorectal Lotion

Drug Facts

Active ingredient

Pramoxine HCL 1% w/w

Purpose

Local Anesthetic

Use

- for the temporary relief of itching and discomfort in the perianal area.

Warnings

for external use only.

Do not

- exceed the recommended daily dosage unless directed by a Physician.

Do not

- put this product into rectum by using fingers or any applicator.

Stop use and ask a Physician if

- Condition worsens
- Symptoms do not improve in 7 days
- Allergic reactions develop to ingredients in this product
- Symptoms being treated do not improve or subsideor if redness, irritation, swelling, pain, bleeding or other symptoms develop or increase

KEEP OUT OF REACH OF CHILDREN

Keep this product out of the reach of children. If swallowed, get medical attention or contact a Poison Control Center right away.

Directions

- Shake well before using.
- When practical, cleansethe affected area with mild soap and warm water and rinse thoroughly.
- Gently dry by patting or blotting with toilet tissue or a soft cloth before application of this product.
- Adults and children 12 years of age and older: apply to affected area up to five times daily.
- Children under 12 years of age, consult a Physician.

Inactive ingredients

Carbomer 940, Cetyl Alcohol, Di-isopropyl Adipate, Dimethicone, Glycerin 99.7%, Lanolin Anhydrous, Light Mineral Oil, PEG 40 Stearate, Potassium Sorbate, Purified Water, Sorbic Acid, Stearic Acid, Stearyl Alcohol, Trolamine, Ultimate White Petrolatum.

Questions or comments?

Call us at: 1-800-442-7882

Distributed by:
STRATUS
PHARMACEUTICALS INC
Miami, Florida 33186

PRINCIPAL DISPLAY PANEL - 118 mL Bottle Box

NDC 58980-522-40

ANORECTAL

PRAMOXINE
HYDROCHLORIDE 1%

ANORECTAL

FAST RELIEF FROM ITCH
AND DISCOMFORT

ANORECTAL
(hemorrhoidal)
LOTION

Net 4 fl oz (118 mL)